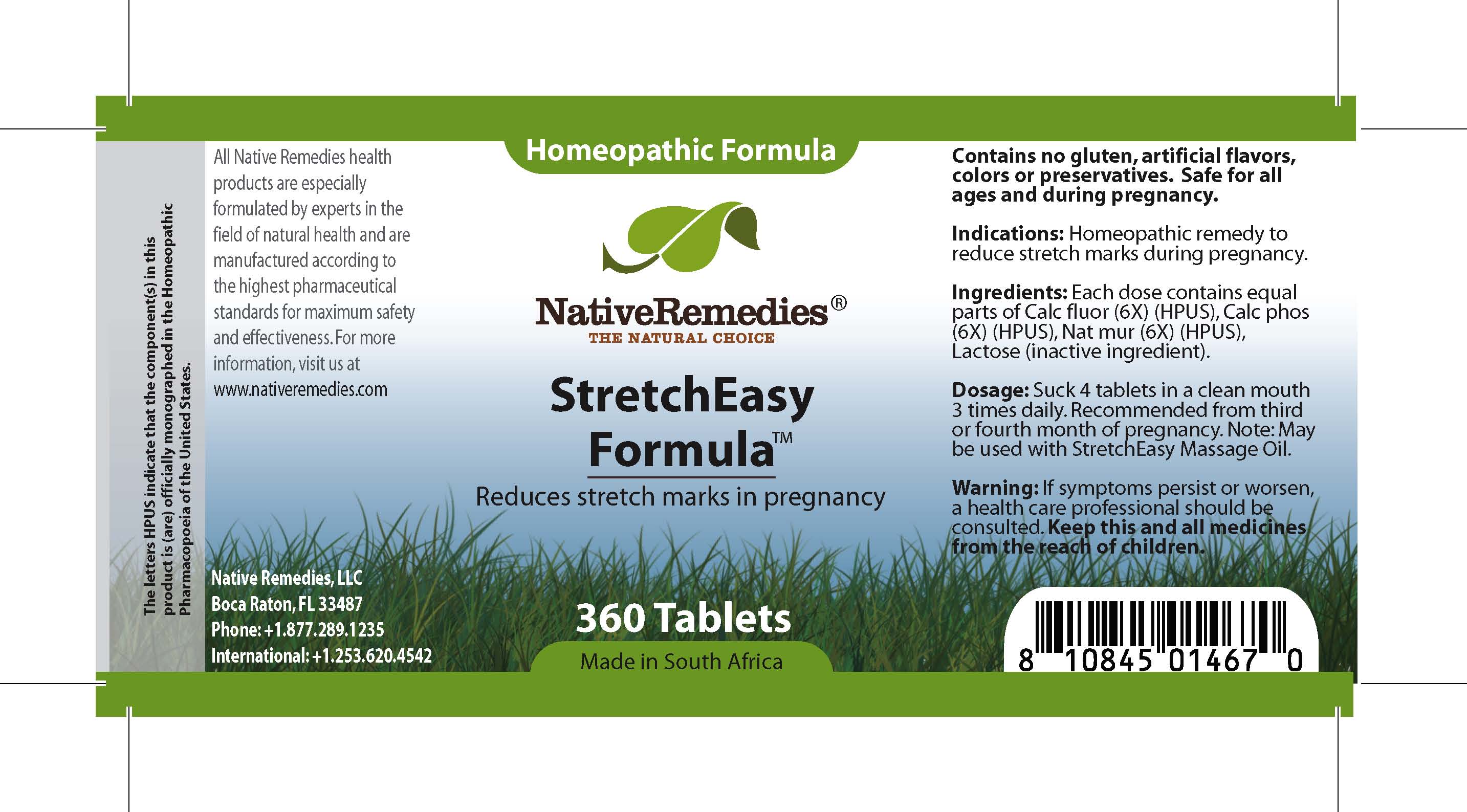 DRUG LABEL: StretchEasy Formula
NDC: 68647-200 | Form: TABLET
Manufacturer: Feelgood Health
Category: homeopathic | Type: HUMAN OTC DRUG LABEL
Date: 20100928

ACTIVE INGREDIENTS: CALCIUM FLUORIDE 6 [hp_X]/1 1; ANHYDROUS DIBASIC CALCIUM PHOSPHATE 6 [hp_X]/1 1; SODIUM CHLORIDE 6 [hp_X]/1 1
INACTIVE INGREDIENTS: LACTOSE

STRETCHEASY FORMULA

PURPOSE

Reduces stretch marks in pregnancy

INDICATIONS AND USAGE

Indications: Homeopathic remedy to reduce stretch marks during pregnancy.

DOSAGE AND ADMINISTRATION

Dosage: Dissolve 4 tablets in a clean mouth 3 times daily. Recommended from third or fourth month of pregnancy. May be used with StretchEasy Massage Oil™.

GENERAL PRECAUTIONS

Caution: If symptoms persist or worsen, a health care professional should be consulted. Keep this and all medicines from the reach of children.

ACTIVE INGREDIENT

Ingredients: Each dose contains equal parts of Calc fluor (6X) (HPUS), Calc phos (6X) (HPUS), Nat mur (6X) (HPUS)

Lactose (inactive ingredient).

WARNINGS

Contains no gluten, artificial flavors, colors or preservatives.Safe for all ages and during pregnancy.

PATIENT COUNSELING INFORMATION

All Native Remedies health products are especially formulated by experts in the field of natural health and are manufactured according to the highest pharmaceutical standards for maximum safety and effectiveness. For more information, visit us at www.nativeremedies.com

Distributed by

Native Remedies, LLC

6531 Park of Commerce Blvd.

Suite 160

Boca Raton, FL 33487

Phone: 1.877.289.1235

International: + 1.561.999.8857

The letters HPUS indicate that the component(s) in this product is (are) officially monographed in the Homeopathic Pharmacopoeia of the United States.

KEEP OUT OF REACH OF CHILDREN

Keep this and all medicines from the reach of children.